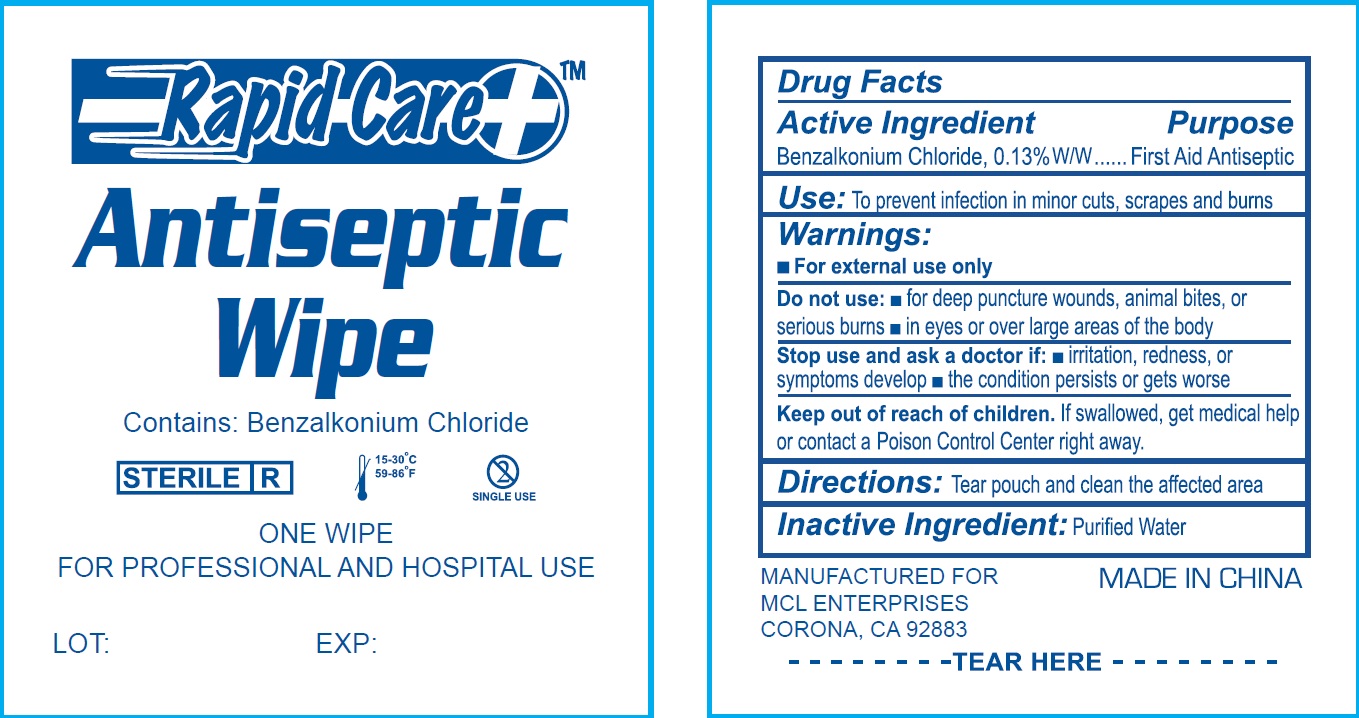 DRUG LABEL: Antiseptic
NDC: 71622-001 | Form: SWAB
Manufacturer: MCL Enterprises
Category: otc | Type: HUMAN OTC DRUG LABEL
Date: 20171228

ACTIVE INGREDIENTS: BENZALKONIUM CHLORIDE 1.3 mg/1 g
INACTIVE INGREDIENTS: WATER

Antiseptic Wipe

Active Ingredient

Benzalkonium Chloride, 0.13% W/W

Purpose

First Aid Antiseptic

Use:

To prevent infection in minor cuts, scrapes and burns

Warnings:

- For external use only

Do not use:

- for deep puncture wounds, animal bites, or serious burns.
- in eyes or over large areas of the body

Stop use and ask a doctor if:

- irritation, redness, or symptoms develop
- the condition persists or gets worse

Keep out of reach of children.

If swallowed, get medical help or contact a Poison Control Center right away.

Directions:

Tear pouch and clean the affected area

Inactive Ingredient:

Purified Water